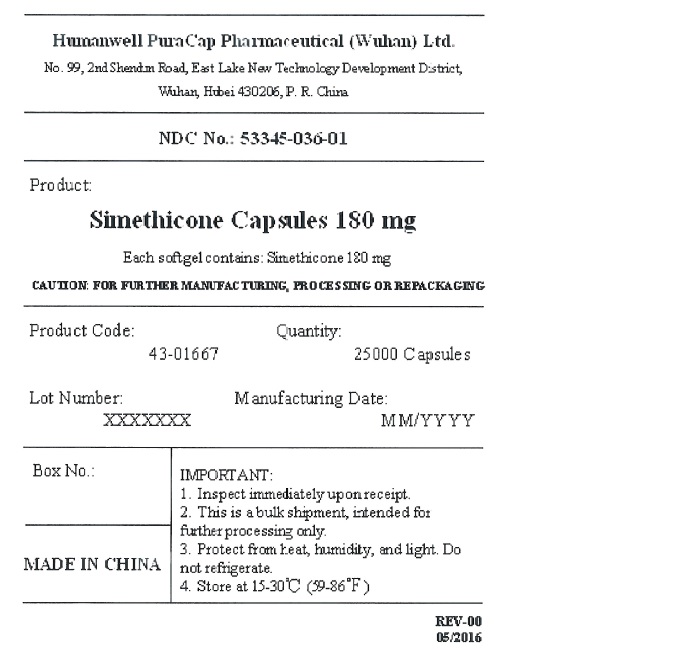 DRUG LABEL: Simethicone
NDC: 53345-036 | Form: CAPSULE, LIQUID FILLED
Manufacturer: Humanwell PuraCap Pharmaceutical (Wuhan) Co., Ltd
Category: otc | Type: HUMAN OTC DRUG LABEL
Date: 20241125

ACTIVE INGREDIENTS: DIMETHICONE 180 mg/1 1
INACTIVE INGREDIENTS: FD&C YELLOW NO. 6; GELATIN; GLYCERIN; WATER

Simethicone Capsules 180 mg

Active ingredient (in each capsule)

Simethicone 180 mg

Purpose

Anti-gas

Uses

- relieves bloating, pressure or fullness commonly referred to as gas

Warnings

Stop use and ask a doctorifcondition persists

Keep out of reach of children.

Directions

- swallow one or two softgels as needed after a meal
- do not exceed two softgels per day except under the advice and supervision of a physician

Other information

- store at room temperature 59º - 86ºF (15º - 30ºC)

Inactive ingredients

FD&C yellow#6, gelatin, glycerin, purified water and white edible ink

PRINCIPAL DISPLAY PANEL - Shipping Label

SIMETHICONE CAPSULES, 180 mg

Quantity : 25000 Capsules
NDC. No : 53345-036-01

IMPORTANT:

1. Inspect immediate upon receipt.
2. This is a bulk shipment, intended for further processing only.
3. Protect from heat, humidity, and light. Do not refrigerate.
4. Store at 15-30°C (59-86°F)

CAUTION : FOR FURTHER MANUFACTURING, PROCESSING OR REPACKAGING